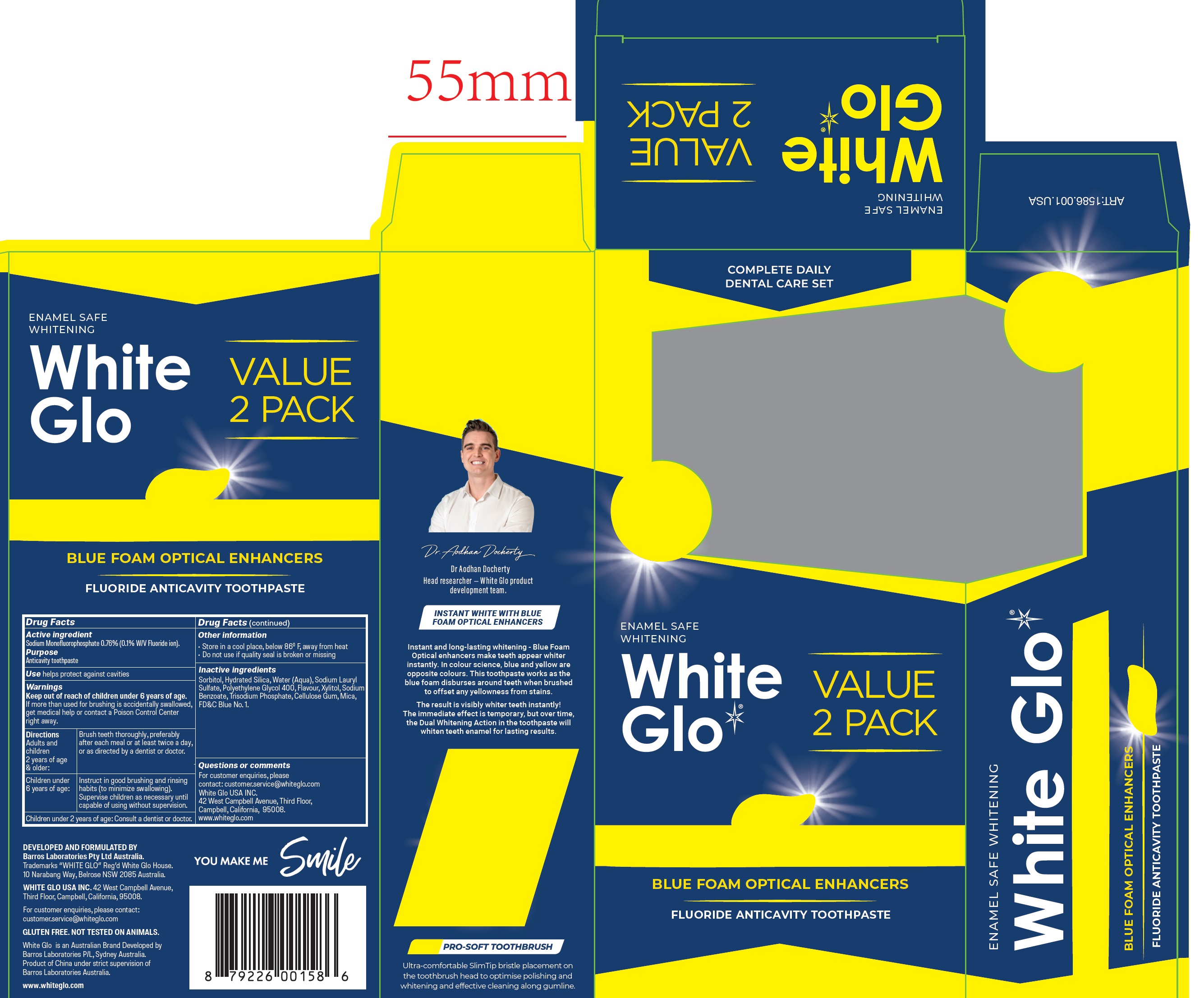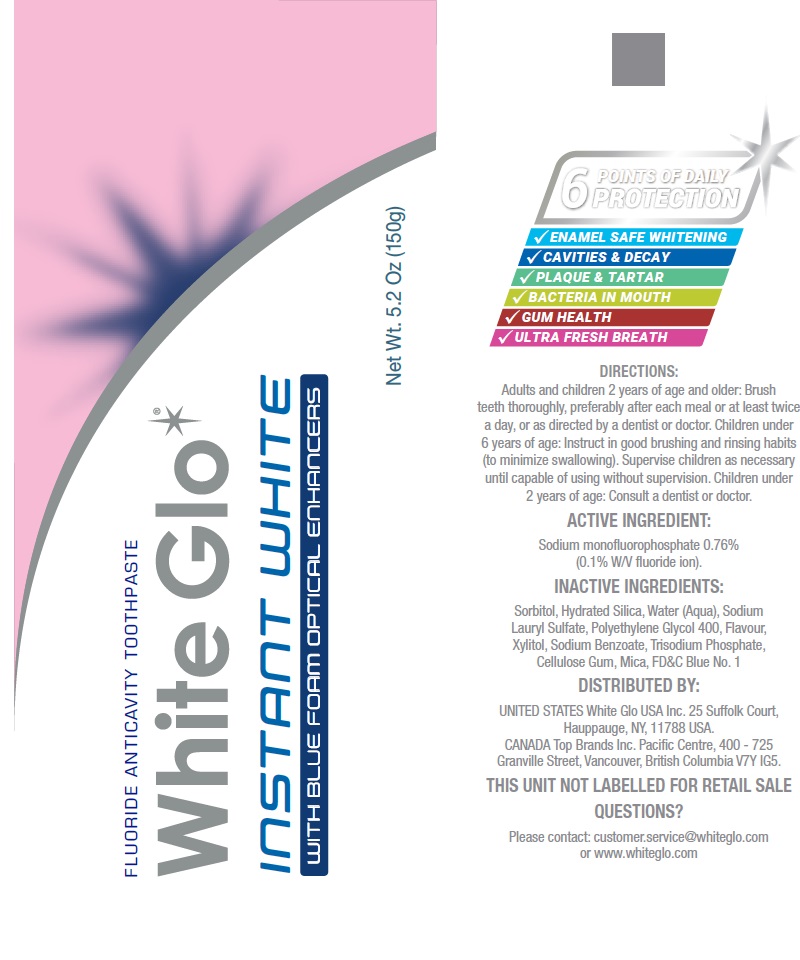 DRUG LABEL: White Glo Instant White Blue Foam Optical Enhancers Fluoride Anticavity Value 2 pack and Toothbrush
NDC: 73656-028 | Form: KIT | Route: DENTAL
Manufacturer: WHITE GLO USA INC
Category: otc | Type: HUMAN OTC DRUG LABEL
Date: 20250226

ACTIVE INGREDIENTS: SODIUM MONOFLUOROPHOSPHATE 7.6 mg/1 g
INACTIVE INGREDIENTS: SORBITOL; HYDRATED SILICA; WATER; SODIUM LAURYL SULFATE; POLYETHYLENE GLYCOL 400; XYLITOL; SODIUM BENZOATE; CARBOXYMETHYLCELLULOSE SODIUM, UNSPECIFIED; MICA; FD&C BLUE NO. 1

White Glo Instant White Blue Foam Optical Enhancers Fluoride Anticavity Toothpaste Value 2 pack and Toothbrush

Active ingredient

Sodium Monofluorophosphate 0.76% (0.1% W/V Fluoride ion).

Purpose

Anticavity toothpaste

Use

helps protect against cavities

Warnings

Keep out of reach of children

under 6 years of age.

If more than used for brushing is accidentally swallowed, get medical help or contact a Poison Control Center right away.

Directions

Adults and children 2 years of age & older: | Brush teeth thoroughly, preferably after each meal or at least twice a day, or as directed by a dentist or doctor.
Children under 6 years of age: | Instruct in good brushing and rinsing habits (to minimize swallowing). Supervise children as necessary until capable of using without supervision.

Children under 2 years of age: Consult a dentist or doctor.

Other information

- Store in a cool place, below 86° F, away from heat
- Do not use if quality seal is broken or missing

Inactive ingredients

Sorbitol, Hydrated Silica, Water (Aqua), Sodium Lauryl Sulfate, Polyethylene Glycol 400, Flavour, Xylitol, Sodium Benzoate, Trisodium Phosphate, Cellulose Gum, Mica, FD&C Blue No. 1.

Questions or comments

For customer enquiries, please contact: customer.service@whiteglo.com